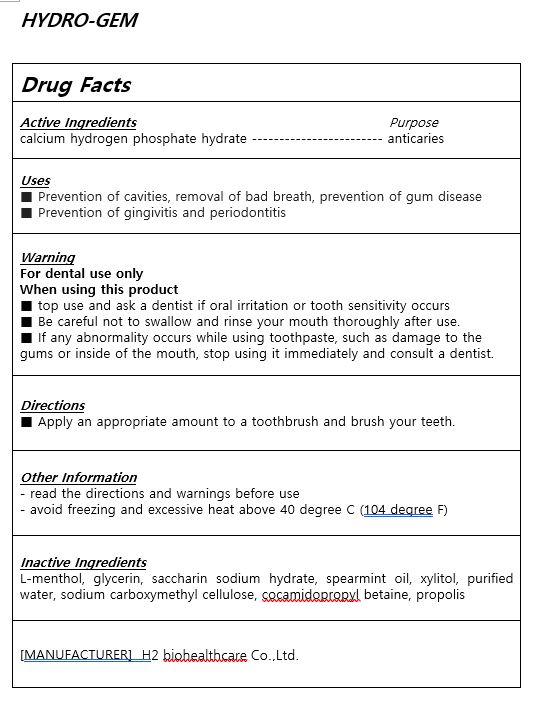 DRUG LABEL: HYDROGEMToothpaste
NDC: 83811-0001 | Form: PASTE, DENTIFRICE
Manufacturer: H2 biohealthcare Co.,Ltd
Category: otc | Type: HUMAN OTC DRUG LABEL
Date: 20231119

ACTIVE INGREDIENTS: CALCIUM PHOSPHATE, DIBASIC, ANHYDROUS 2.14 g/100 g
INACTIVE INGREDIENTS: XYLITOL; WATER

ACTIVE INGREDIENT

calcium hydrogen phosphate hydrate

PURPOSE

■ Prevention of cavities, removal of bad breath, prevention of gum disease

■ Prevention of gingivitis and periodontitis

Keep out of reach of children

INDICATIONS AND USAGE

apply appropriate amount of the tooth paste on the tooth brush and brush the teeth

WARNINGS

For dental use only

When using this product

■ top use and ask a dentist if oral irritation or tooth sensitivity occurs

■ Be careful not to swallow and rinse your mouth thoroughly after use.

■ If any abnormality occurs while using toothpaste, such as damage to the gums or inside of the mouth, stop using it immediately and consult a dentist.

INACTIVE INGREDIENT

L-menthol, glycerin, saccharin sodium hydrate, spearmint oil, xylitol, purified water, sodium carboxymethyl cellulose, cocamidopropyl betaine, propolis

DOSAGE AND ADMINISTRATION

For dental use only